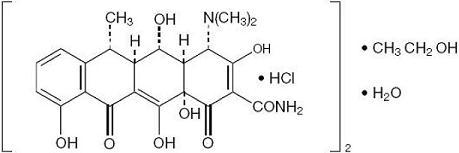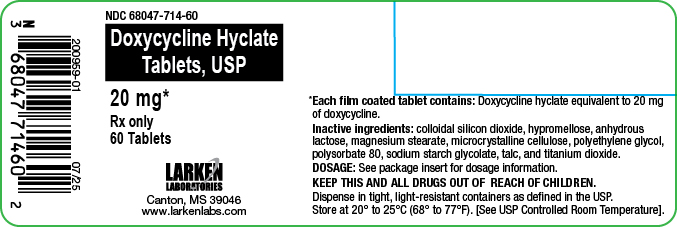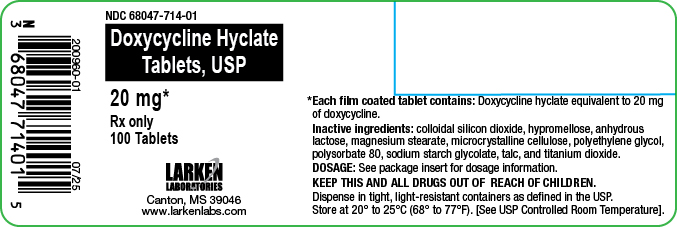 DRUG LABEL: Doxycycline Hyclate
NDC: 68047-714 | Form: TABLET
Manufacturer: Larken Laboratories, Inc.
Category: prescription | Type: HUMAN PRESCRIPTION DRUG LABEL
Date: 20250731

ACTIVE INGREDIENTS: DOXYCYCLINE HYCLATE 20 mg/1 1
INACTIVE INGREDIENTS: SILICON DIOXIDE; HYPROMELLOSE 2910 (3 MPA.S); HYPROMELLOSE 2910 (6 MPA.S); ANHYDROUS LACTOSE; MAGNESIUM STEARATE; CELLULOSE, MICROCRYSTALLINE; POLYETHYLENE GLYCOL 400; POLYSORBATE 80; SODIUM STARCH GLYCOLATE TYPE A POTATO; TALC; TITANIUM DIOXIDE

DOXYCYCLINE HYCLATE TABLETS, USP

(doxycycline hyclate tablets) 20 mg
Rev. 07/25

DESCRIPTION

Doxycycline hyclate is available as a 20 mg tablet formulation of doxycycline for oral administration.

The structural formula of doxycycline hyclate is:

with an empirical formula of (C22H24N2O8•HCl)2•C2H6O•H2O and a molecular weight of 1025.89. The chemical designation for doxycycline is 4-(dimethylamino)-1, 4, 4a, 5, 5a, 6, 11, 12a–octahydro-3, 5, 10, 12, 12a–octahydro-3, 5, 10, 12, 12a-pentahydroxy-6-methyl-1, 11-dioxo-2-naphthacenecarboxamide monohydrochloride, compound with ethyl alcohol (2:1), monohydrate.

Doxycycline hyclate is a yellow to light-yellow crystalline powder which is soluble in water.

Inactive Ingredients:

Inactive ingredients in the formulation are: colloidal silicon dioxide, hypromellose, anhydrous lactose, magnesium stearate, microcrystalline cellulose, polyethylene glycol, polysorbate 80, sodium starch glycolate, talc, and titanium dioxide. Each tablet contains 23 mg of doxycycline hyclate equivalent to 20 mg of doxycycline.

CLINICAL PHARMACOLOGY

After oral administration, doxycycline hyclate is rapidly and nearly completely absorbed from the gastrointestinal tract. Doxycycline is eliminated with a half-life of approximately 18 hours by renal and fecal excretion of unchanged drug.

Mechanism of Action:

Doxycycline has been shown to inhibit collagenase activity in vitro.^1Additional studies have shown that doxycycline reduces the elevated collagenase activity in the gingival crevicular fluid of patients with adult periodontitis.^2,3The clinical significance of these findings is not known.

Microbiology:

Doxycycline is a member of the tetracycline class of antibiotics. The dosage of doxycycline achieved with this product during administration is well below the concentration required to inhibit microorganisms commonly associated with adult periodontitis. Clinical studies with this product demonstrated no effect on total anaerobic and facultative bacteria in plaque samples from patients administered this dose regimen for 9 to 18 months. This product should notbe used for reducing the numbers of or eliminating those microorganisms associated with periodontitis.

Pharmacokinetics

The pharmacokinetics of doxycycline following oral administration of doxycycline hyclate were investigated in 4 volunteer studies involving 107 adults. Additionally, doxycycline pharmacokinetics have been characterized in numerous scientific publications.^4Pharmacokinetic parameters for doxycycline hyclate following single oral doses and at steady-state in healthy subjects are presented as follows:

Pharmacokinetic Parameters for Doxycycline Hyclate
 | n | Cmax [Mean ± SD] (ng/mL) | Tmax [Mean and range] (hr) | Cl/F (L/hr) | t1/2 (hr)
Single dose 20 mg (tablet) | 20 | 362±101 | 1.4 (1.0-2.5) | 3.85±1.3 | 18.1±4.85
Steady-State 20 mg BID [Steady-State data were obtained from normal volunteers administered a bioequivalent formulation.] | 30 | 790±285 | 2 (0.98-12.0) | 3.76±1.06 | Not Determined

Absorption:Doxycycline is well absorbed after oral administration. In a single-dose study, concomitant administration of doxycycline hyclate with a 1000 calorie, high-fat, high-protein meal which included dairy products, in healthy volunteers, resulted in a decrease in the rate and extent of absorption and delay in the time to maximum concentrations.

Distribution:Doxycycline is greater than 90% bound to plasma proteins. Its apparent volume of distribution is variously reported as between 52.6 and 134 L.^4,6

Metabolism:Major metabolites of doxycycline have not been identified. However, enzyme inducers such as barbiturates, carbamazepine, and phenytoin decrease the half-life of doxycycline.

Excretion:Doxycycline is excreted in the urine and feces as unchanged drug. It is variously reported that between 29% and 55.4% of an administered dose can be accounted for in the urine by 72 hours.^5,6Half-life averaged 18 hours in subjects receiving a single 20 mg doxycycline dose.

Special Populations

Geriatric:Doxycycline pharmacokinetics have not been evaluated in geriatric patients.

Pediatric:Doxycycline pharmacokinetics have not been evaluated in pediatric patients (See WARNINGSsection).

Gender:Doxycycline pharmacokinetics were compared in 9 men and 11 women under fed and fasted conditions. While female subjects had a higher rate (Cmax) and extent of absorption (AUC), these differences are thought to be due to differences in body weight/lean body mass. Differences in other pharmacokinetic parameters were not significant.

Race:Differences in doxycycline pharmacokinetics among racial groups have not been evaluated.

Renal Insufficiency:Studies have shown no significant difference in serum half-life of doxycycline in patients with normal and severely impaired renal function. Hemodialysis does not alter the half-life of doxycycline.

Hepatic Insufficiency:Doxycycline pharmacokinetics have not been evaluated in patients with hepatic insufficiency.

Drug Interactions:(See PRECAUTIONSsection)

Clinical Study

In a randomized, multi-centered, double-blind, 9-month Phase 3 study involving 190 adult patients with periodontal disease [at least two probing sites per quadrant of between 5 and 9 mm pocket depth (PD) and attachment level (ALv)], the effects of oral administration of 20 mg twice a day of doxycycline hyclate (using a bioequivalent capsule formulation) plus scaling and root planing (SRP) were compared to placebo control plus SRP. Both treatment groups were administered a course of scaling and root planing in 2 quadrants at Baseline. Measurements of ALv, PD and bleeding-on-probing (BOP) were obtained at Baseline, 3, 6, and 9 months from each site about each tooth in the two quadrants that received SRP using the UNC-15 manual probe. Each tooth site was categorized into one of three strata based on Baseline PD: 0-3 mm (no disease), 4-6 mm (mild/moderate disease), ≥ 7 mm (severe disease). For each stratum and treatment group, the following were calculated at month 3, 6, and 9: mean change in ALv from baseline, mean change in PD from baseline, mean percentage of tooth sites per patient exhibiting attachment loss of ≥ 2 mm from baseline, and percentage of tooth sites with bleeding on probing. The results are summarized in the following table.

Clinical Results at Nine Months of Doxycycline Hyclate Capsules, 20 mg, as an Adjunct to SRP(Bioequivalent to Doxycycline Hyclate Tablets, 20 mg)
Parameter | Baseline Pocket Depth
 | 0-3 mm | 4-6 mm | ≥ 7 mm
Number of Patients (Doxycycline Hyclate 20mg BID) | 90 | 90 | 79
Number of Patients (Placebo) | 93 | 93 | 78
Mean Gain (SD) in ALv [Alv=Clinical Attachment Level]
Doxycycline hyclate 20 mg BID | 0.25 (0.29) mm | 1.03 (0.47) mm [p<0.050 vs. the placebo control group.] | 1.55 (1.16)mm
Placebo | 0.20 (0.29) mm | 0.86 (0.48) mm | 1.17 (1.15) mm
Mean Decrease (SD [SD=Standard Deviation]) in PD [PD=Pocket Depth]
Doxycycline hyclate 20 mg BID | 0.16 (0.19) mm [p<0.010 vs. the placebo control group.] | 0.95 (0.47) mm | 1.68 (1.07)mm
Placebo | 0.05 (0.19) mm | 0.69 (0.48) mm | 1.20 (1.06) mm
% of Sites (SD) with loss of ALv ≥ 2 mm
Doxycycline hyclate 20 mg BID | 1.9 (4.2)% | 1.3 (4.5)% | 0.3 (9.4)%
Placebo | 2.2 (4.1)% | 2.4 (4.4)% | 3.6 (9.4)%
% of Sites (SD) with BOP [BOP=Bleeding on Probing]
Doxycycline hyclate 20 mg BID | 39 (19)% | 64 (18)% | 75 (29)%
Placebo | 46 (19)% | 70 (18)% | 80 (29)%

INDICATIONS AND USAGE

Doxycycline Hyclate is indicated for use as an adjunct to scaling and root planing to promote attachment level gain and to reduce pocket depth in patients with adult periodontitis.

CONTRAINDICATIONS

This drug is contraindicated in persons who have shown hypersensitivity to doxycycline or any of the other tetracyclines.

WARNINGS

THE USE OF DRUGS OF THE TETRACYCLINE CLASS DURING TOOTH DEVELOPMENT (LAST HALF OF PREGNANCY, INFANCY AND CHILDHOOD TO THE AGE OF 8 YEARS) MAY CAUSE PERMANENT DISCOLORATION OF THE TEETH (YELLOW-GRAY-BROWN).

This adverse reaction is more common during long-term use of the drugs but has been observed following repeated short-term courses. Enamel hypoplasia has also been reported. TETRACYCLINE DRUGS, THEREFORE, SHOULD NOT BE USED IN THIS AGE GROUP AND IN PREGNANT OR NURSING MOTHERS UNLESS THE POTENTIAL BENEFITS MAY BE ACCEPTABLE DESPITE THE POTENTIAL RISKS.

All tetracyclines form a stable calcium complex in any bone forming tissue. A decrease in fibula growth rate has been observed in premature infants given oral tetracyclines in doses of 25 mg/kg every 6 hours. This reaction was shown to be reversible when the drug was discontinued.

Doxycycline can cause fetal harm when administered to a pregnant woman. Results of animal studies indicate that tetracyclines cross the placenta, are found in fetal tissues, and can have toxic effects on the developing fetus (often related to retardation of skeletal development). Evidence of embryotoxicity has also been noted in animals treated early in pregnancy. If any tetracyclines are used during pregnancy, or if the patient becomes pregnant while taking this drug, the patient should be apprised of the potential hazard to the fetus. The catabolic action of the tetracyclines may cause an increase in BUN. Previous studies have not observed an increase in BUN with the use of doxycycline in patients with impaired renal function.

Photosensitivity manifested by an exaggerated sunburn reaction has been observed in some individuals taking tetracyclines. Patients apt to be exposed to direct sunlight or ultraviolet light should be advised that this reaction can occur with tetracycline drugs, and treatment should be discontinued at the first evidence of skin erythema.

Fixed drug eruptions have occurred with doxycycline and have been associated with worsening severity upon subsequent administrations, including generalized bullous fixed drug eruption (see Adverse Reactions for Tetracyclines).

If severe skin reactions occur, discontinue Doxycycline Hyclate tablets immediately and institute appropriate therapy.

Adverse Reactions for Tetracyclines: Skin: Maculopapular and erythematous rashes, and fixed drug eruption have been reported. Exfoliative dermatitis has been reported but is uncommon. Photosensitivity is discussed above (see WARNINGS section).

PRECAUTIONS

GENERAL PRECAUTIONS

While no overgrowth by opportunistic microorganisms such as yeast were noted during clinical studies, as with other antimicrobials, doxycycline hyclate therapy may result in overgrowth of non-susceptible microorganisms including fungi.

The use of tetracyclines may increase the incidence of vaginal candidiasis.

Doxycycline Hyclate should be used with caution in patients with a history or predisposition to oral candidiasis. The safety and effectiveness of Doxycycline Hyclate has not been established for the treatment of periodontitis in patients with coexistent oral candidiasis.

If superinfection is suspected, appropriate measures should be taken.

Laboratory Tests:

In long term therapy, periodic laboratory evaluations of organ systems, including hematopoietic, renal, and hepatic studies should be performed.

Drug Interactions

Because tetracyclines have been shown to depress plasma prothrombin activity, patients who are on anticoagulant therapy may require downward adjustment of their anticoagulant dosage.

Since bacterial antibiotics, such as the tetracycline class of antibiotics, may interfere with the bactericidal action of members of the β-lactam (e.g. penicillin) class of antibiotics, it is not advisable to administer these antibiotics concomitantly.

Absorption of tetracyclines is impaired by antacids containing aluminum, calcium, or magnesium, and iron containing preparations, and by bismuth subsalicylate.

Barbiturates, carbamazepine, and phenytoin decrease the half-life of doxycycline.

The concurrent use of tetracycline and methoxyflurane has been reported to result in fatal renal toxicity.

Concurrent use of tetracyclines may render oral contraceptives less effective.

Drug/Laboratory Test Interactions

False elevations of urinary catecholamine levels may occur due to interference with the fluorescence test.

Carcinogenesis, Mutagenesis, Impairment of Fertility:

Doxycycline hyclate was assessed for potential to induce carcinogenesis in a study in which the compound was administered to Sprague-Dawley rats by gavage at dosages of 20, 75, and 200 mg/kg/day for two years. An increased incidence of uterine polyps was observed in female rats that received 200 mg/kg/day, a dosage that resulted in a systemic exposure to doxycycline approximately nine times that observed in female humans that used doxycycline hyclate (exposure comparison based upon AUC values). No impact upon tumor incidence was observed in male rats at 200 mg/kg/day, or in either gender at the other dosages studied. Evidence of oncogenic activity was obtained in studies with related compounds, i.e., oxytetracycline (adrenal and pituitary tumors), and minocycline (thyroid tumors).

Doxycycline hyclate demonstrated no potential to cause genetic toxicity in an in vitropoint mutation study with mammalian cells (CHO/HGPRT forward mutation assay) or in an in vivo micronucleus assay conducted in CD-1 mice. However, data from an in vitroassay with CHO cells for potential to cause chromosomal aberrations suggest that doxycycline hyclate is a weak clastogen.

Oral administration of doxycycline hyclate to male and female Sprague-Dawley rats adversely affected fertility and reproductive performance, as evidenced by increased time for mating to occur, reduced sperm motility, velocity, and concentration, abnormal sperm morphology, and increased pre- and post-implantation losses. Doxycycline hyclate induced reproductive toxicity at all dosages that were examined in this study, as even the lowest dosage tested (50 mg/kg/day) induced a statistically significant reduction in sperm velocity. Note that 50 mg/kg/day is approximately 10 times the amount of doxycycline hyclate contained in the recommended daily dose of doxycycline hyclate for a 60 kg human when compared on the basis of body surface area estimates (mg/m^2). Although doxycycline impairs the fertility of rats when administered at sufficient dosage, the effect of doxycycline hyclate on human fertility is unknown.

Pregnancy

Teratogenic Effects:

(See WARNINGSsection). Results from animal studies indicate that doxycycline crosses the placenta and is found in fetal tissues.

Nonteratogenic effects

(See WARNINGS section).

Labor and Delivery

The effect of tetracyclines on labor and delivery is unknown.

Nursing Mothers

Tetracyclines are excreted in human milk. Because of the potential for serious adverse reactions in nursing infants from doxycycline, the use of doxycycline hyclate in nursing mothers is contraindicated. (See WARNINGS section).

Pediatric Use

The use of doxycycline hyclate in infancy and childhood is contraindicated. (See WARNINGSsection.)

ADVERSE REACTIONS

sdverse Reactions in Clinical Trials of a bioequivalent form of doxycycline hyclate capsules:In clinical trials of adult patients with periodontal disease 213 patients received 20 mg BID over a 9 - 12 month period. The most frequent adverse reactions occurring in studies involving treatment with a bioequivalent form of doxycycline hyclate capsules or placebo are listed below:

Incidence (%) of Adverse Reactions in Clinical Trials of Doxycycline Hyclate Capsules, 20 mg(Bioequivalent to Doxycycline Hyclate Tablets, 20 mg) vs. Placebo
Adverse Reaction | Doxycycline Hyclate Capsules 20 mg BID (n=213) | Placebo (n=215)
Headache | 55 (26%) | 56 (26%)
Common Cold | 47 (22%) | 46 (21%)
Flu Symptoms | 24 (11%) | 40 (19%)
Tooth Ache | 14 (7%) | 28 (13%)
Periodontal Abscess | 8 (4%) | 21 (10%)
Tooth Disorder | 13 (6%) | 19 (9%)
Nausea | 17 (8%) | 12 (6%)
Sinusitis | 7 (3%) | 18 (8%)
Injury | 11 (5%) | 18 (8%)
Dyspepsia | 13 (6%) | 5 (2%)
Sore Throat | 11 (5%) | 13 (6%)
Joint Pain | 12 (6%) | 8 (4%)
Diarrhea | 12 (6%) | 8 (4%)
Sinus Congestion | 11 (5%) | 11 (5%)
Coughing | 9 (4%) | 11 (5%)
Sinus Headache | 8 (4%) | 8 (4%)
Rash | 8 (4%) | 6 (3%)
Back Pain | 7 (3%) | 8 (4%)
Back Ache | 4 (2%) | 9 (4%)
Menstrual Cramp | 9 (4%) | 5 (2%)
Acid Indigestion | 8 (4%) | 7 (3%)
Pain | 8 (4%) | 5 (2%)
Infection | 4 (2%) | 6 (3%)
Gum Pain | 1(<1%) | 6 (3%)
Bronchitis | 7 (3%) | 5 (2%)
Muscle Pain | 2 (1%) | 6 (3%)
Note: Percentages are based on total number of study participants in each treatment group.

Adverse Reactions for Tetracyclines:The following adverse reactions have been observed in patients receiving tetracyclines:

Gastrointestinal: anorexia, nausea, vomiting, diarrhea, glossitis, dysphagia, enterocolitis, and inflammatory lesions (with vaginal candidiasis) in the anogenital region. Hepatotoxicity has been reported rarely. Rare instances of esophagitis and esophageal ulcerations have been reported in patients receiving the capsule forms of the drugs in the tetracycline class. Most of these patients took medications immediately before going to bed. (See DOSAGE AND ADMINISTRATION section).

Skin: maculopapular and erythematous rashes. Exfoliative dermatitis has been reported but is uncommon. Photosensitivity is discussed above. (See WARNINGS section).

Renal toxicity: Rise in BUN has been reported and is apparently dose related. (See WARNINGS section).

Hypersensitivity reactions: urticaria, angioneurotic edema, anaphylaxis, anaphylactoid purpura, serum sickness, pericarditis, and exacerbation of systemic lupus erythematosus.

Blood: Hemolytic anemia, thrombocytopenia, neutropenia, and eosinophilia have been reported.

Psychiatric: Depression, anxiety, suicidal ideation, insomnia, abnormal dreams, hallucination.

To report SUSPECTED ADVERSE REACTIONS, contact Larken Laboratories, Inc. at 1-601-855-7678 or FDA at 1-800-FDA-1088 or www.fda.gov/medwatch

OVERDOSAGE

In case of overdosage, discontinue medication, treat symptomatically and institute supportive measures. Dialysis does not alter serum half-life and thus would not be of benefit in treating cases of overdose.

DOSAGE AND ADMINISTRATION

THE DOSAGE OF DOXYCYCLINE HYCLATE DIFFERS FROM THAT OF DOXYCYCLINE USED TO TREAT INFECTIONS. EXCEEDING THE RECOMMENDED DOSAGE MAY RESULT IN AN INCREASED INCIDENCE OF SIDE EFFECTS INCLUDING THE DEVELOPMENT OF RESISTANT MICROORGANISMS.

Doxycycline hyclate 20 mg twice daily as an adjunct following scaling and root planing may be administered for up to 9 months. Doxycycline hyclate should be taken twice daily at 12 hour intervals, usually in the morning and evening. It is recommended that if doxycycline hyclate is taken close to meal times, allow at least one hour prior to or two hours after meals. Safety beyond 12 months and efficacy beyond 9 months have not been established.

Administration of adequate amounts of fluid along with the tablets is recommended to wash down the drug and reduce the risk of esophageal irritation and ulceration. (See ADVERSE REACTIONS section).

HOW SUPPLIED

Doxycycline hyclate are white film coated, round, biconvex tablet, debossed LL714 on one side and plain on the other side containing doxycycline hyclate equivalent to 20 mg doxycycline. Bottle of 60 tablets (NDC 68047-714-60) and Bottle of 100 tablets (NDC 68047-714-01).

Storage and Handling

Store at 20°-25°C (68°-77°F). [See USP Controlled Room Temperature].

Dispense in tight, light-resistant containers (USP).

Manufactured for:

Larken Laboratories, Inc.

Canton, MS 39046

www.larkenlabs.com

201095-01

Rev. 07/25

REFERENCES

1. Golub L.M., Sorsa T., Lee H-M, Ciancio S., Sorbi D., Ramamurthy N.S., Gruber B., Salo T., Konttinen Y.T.: Doxycycline Inhibits Neutrophil (PMN)-type Matrix Metalloproteinases in Human Adult Periodontitis Gingiva. J. Clin. Periodontol 1995; 22: 100-109.
2. Golub L.M., Ciancio S., Ramamurthy N.S., Leung M., McNamara T.F.: low-dose Doxycycline Therapy: Effect on Gingival and Crevicular Fluid Collagenase Activity in Humans. J. Periodont Res 1990; 25: 321-330.
3. Golub L.M., Lee H.M., Greenwald R.A., Ryan M.E., Salo T., Giannobile W.V.: A Matrix Metalloproteinase Inhibitor Reduces Bone-type Collagen Degradation Fragments and Specific Collegenases in Gingival Crevicular Fluid During Adult Periodontitis. Inflammation Research 1997; 46: 310-319.
4. Saivain S., Houin G.: Clinical Pharmacokinetics of Doxycycline and Minocycline. Clin. Pharmacokinetics 1988; 15; 355-366.
5. Schach von Wittenau M., Twomey T.: The Disposition of Doxycycline by Man and Dog. Chemotherapy 1971; 16: 217-228.
6. Campistron G., Coulais Y., Caillard C., Mosser J., Pontagnier H., Houin G.: Pharmacokinetics and Bioavailability of Doxycycline in Humans. Arzneimittel Forschung 1986; 36: 1705-1707.

PACKAGE LABEL.PRINCIPAL DISPLAY PANEL

Figure 2: 60 count Label

Figure 3: 100 count Label